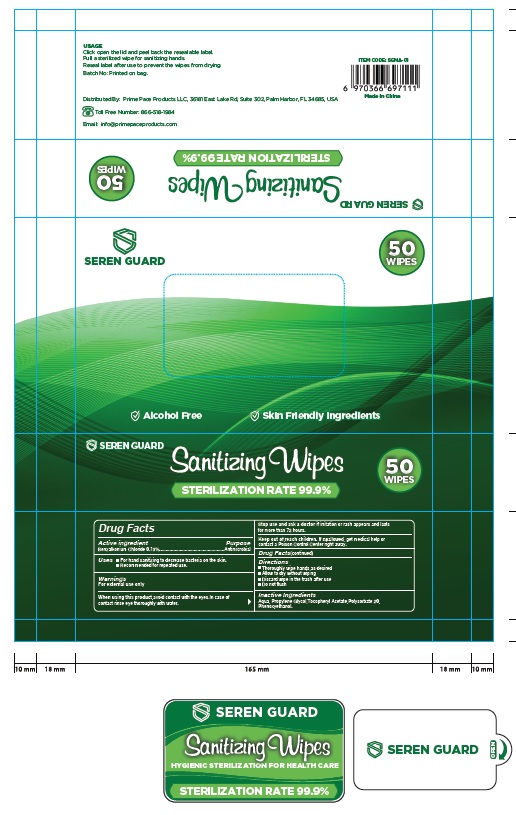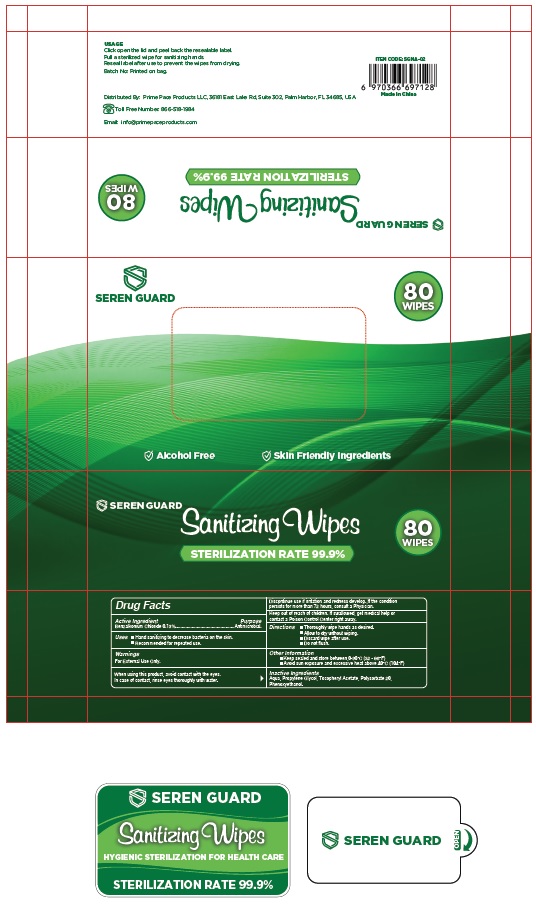 DRUG LABEL: SEREN GUARD
NDC: 79183-001 | Form: PATCH
Manufacturer: Prime Pace Products LLC
Category: otc | Type: HUMAN OTC DRUG LABEL
Date: 20201206

ACTIVE INGREDIENTS: BENZALKONIUM CHLORIDE 0.13 g/100 g
INACTIVE INGREDIENTS: WATER; PROPYLENE GLYCOL; .ALPHA.-TOCOPHEROL ACETATE; POLYSORBATE 20; PHENOXYETHANOL

Drug Facts

Active Ingredient
Benzalkonium Chloride 0.13%

Purpose
Antimicrobial

INDICATIONS AND USAGE

Uses ■ Hand Sanitizer to decrease bacteria on skin.

■ Recommended for repeated use.

Warnings

For external use only.

When using this product keep out of eyes, ears, and mouth.
In case of contact with eyes, rinse eyes thoroughly with water.

STOP USE

Discontinue use if irritation and redness develop. If the condition
persists for more than 72 hours, consult a Physician.

Keep out of reach of children. If swallowed, get medical help or contact a Poison Control Center right away.

DOSAGE AND ADMINISTRATION

Directions ■ Thoroughly wipe hands as desired.
■ Allow to dry without wiping.
■ Discard wipe after use.
■ Do not flush.

Other Information

■ Keep sealed and store between 0-30°C (32 - 86°F)
■ For External Use Only. Avoid sun exposure and excessive heat above 40°C

Inactive ingredients

Aqua, Propylene Glycol, Tocopheryl Acetate, Polysorbate 20,
Phenoxyethanol.

Package Label - Principal Display Panel

SEREN GUARD 80
WIPES

Alcohol Free Skin friendly Ingredients

SEREN GUARD 80
WIPES

Sanitizing Wipes
STERILIZATION RATE 99.9%

USAGE
Click open the lid and peel back the resealable label.
Pull a sterilized wipe for sanitizing hands.
Reseal label after use to prevent the wipes from drying.

Batch No: Printed on bag.

Distributed By: Prime Pace Products LLC, 36181 East Lake Rd, Suite 302, Palm Harbor, FL 34685, USA

Toll Free Number: 866-518-1984

Email: info@primepaceproducts.com

ITEM CODE: SGNA-02

6 970366 697128

Made in China

80 Wipes

50 Wipes

res